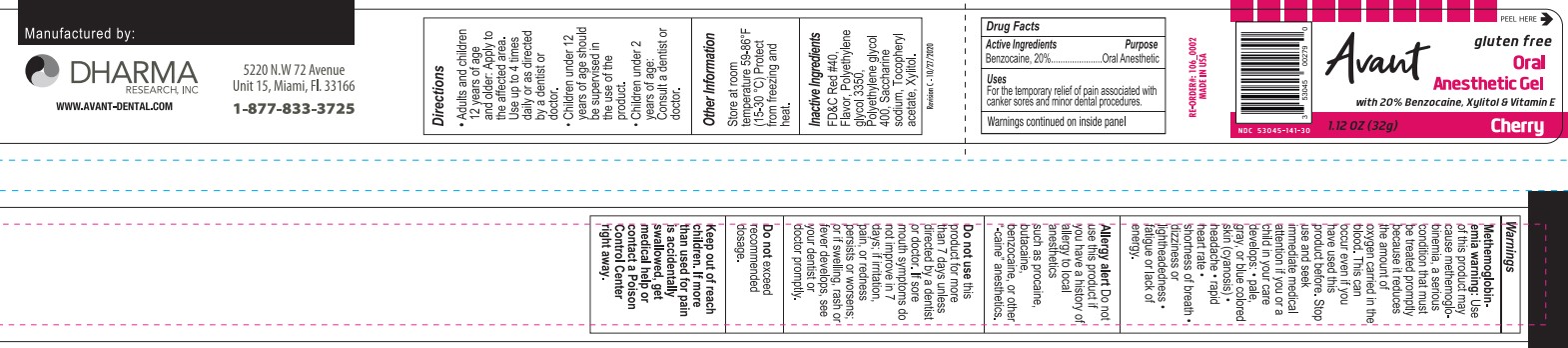 DRUG LABEL: Avant
NDC: 53045-141 | Form: GEL
Manufacturer: Dharma Research, Inc.
Category: otc | Type: HUMAN OTC DRUG LABEL
Date: 20231011

ACTIVE INGREDIENTS: BENZOCAINE 6.4 g/100 g
INACTIVE INGREDIENTS: FD&C RED NO. 40; POLYETHYLENE GLYCOL 3350; POLYETHYLENE GLYCOL 400; SACCHARIN SODIUM; .ALPHA.-TOCOPHEROL ACETATE; XYLITOL

Active Ingredient

Benzocaine, 20%

Purpose

Oral anesthetic

Uses

For the temporary relief of pain associated with canker sores and minor dental procedures.

Warnings

Methemoglobinemia warning

Use of this product may cause methemoglobinemia, a serious condition that must be treated promptly because it reduces the amount of oxygen carried in the blood. This can occur even if you have used this product before.

Stop use and seek medical attention if you or a child in your care develops:
• pale, gray, or blue colored skin (cyanosis)
• headache
• rapid heart rate
• shortness of breath
• dizziness or lightheadedness
• fatigue or lack of energy

DO NOT USE

Alergy alert Do not use this product if you have a history of allergy to local anesthetics such as procaine, butacaine, benzocaine, or other "-caine" anesthetics.

Do not use this product for more than 7 days unless directed by a dentist or doctor. If sore mouth symptoms do not improve in 7 days; if irritation, pain, or redness persists or worsens; or if swelling, rash, or fever develops, see your dentist or doctor promptly.

WARNINGS AND PRECAUTIONS

Do not exceed recommended dosage.

Keep Out of Reach of Children. If more than used for pain is accidentially swallowed, get medical help or contact a Poison Control center right away.

Directions

- Adults and children 2 years of age and older: Apply to the affected area. Use up to 4 times daily or as directed by a dentist or doctor.
- Children under 12 years of age should be supervised in the use of this product
- Children under 2 years of age: Consult a dentist or doctor.

Other Information

Store at room temperature 59-86°F (15-30°C). Protect from freezing and heat.

Inactive Ingredients

FD&C Red No. 40, Flavor, Polyethylene glycol 3350, Polyethylene glycol 400, Saccharine sodium, Tocopheryl acetate, Xylitol

Avant Oral Anesthetic Gel

Gluten Free

with 20% Benzocaine, Xylitol and Vitamin E

1.12 oz (32 g)

Cherry

Manufactured by Dharma Research, Inc., 5220 NW 72nd Ave, Unit 15, Miami, FL 33166

1-877-833-3725

www.avant-dental.com